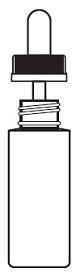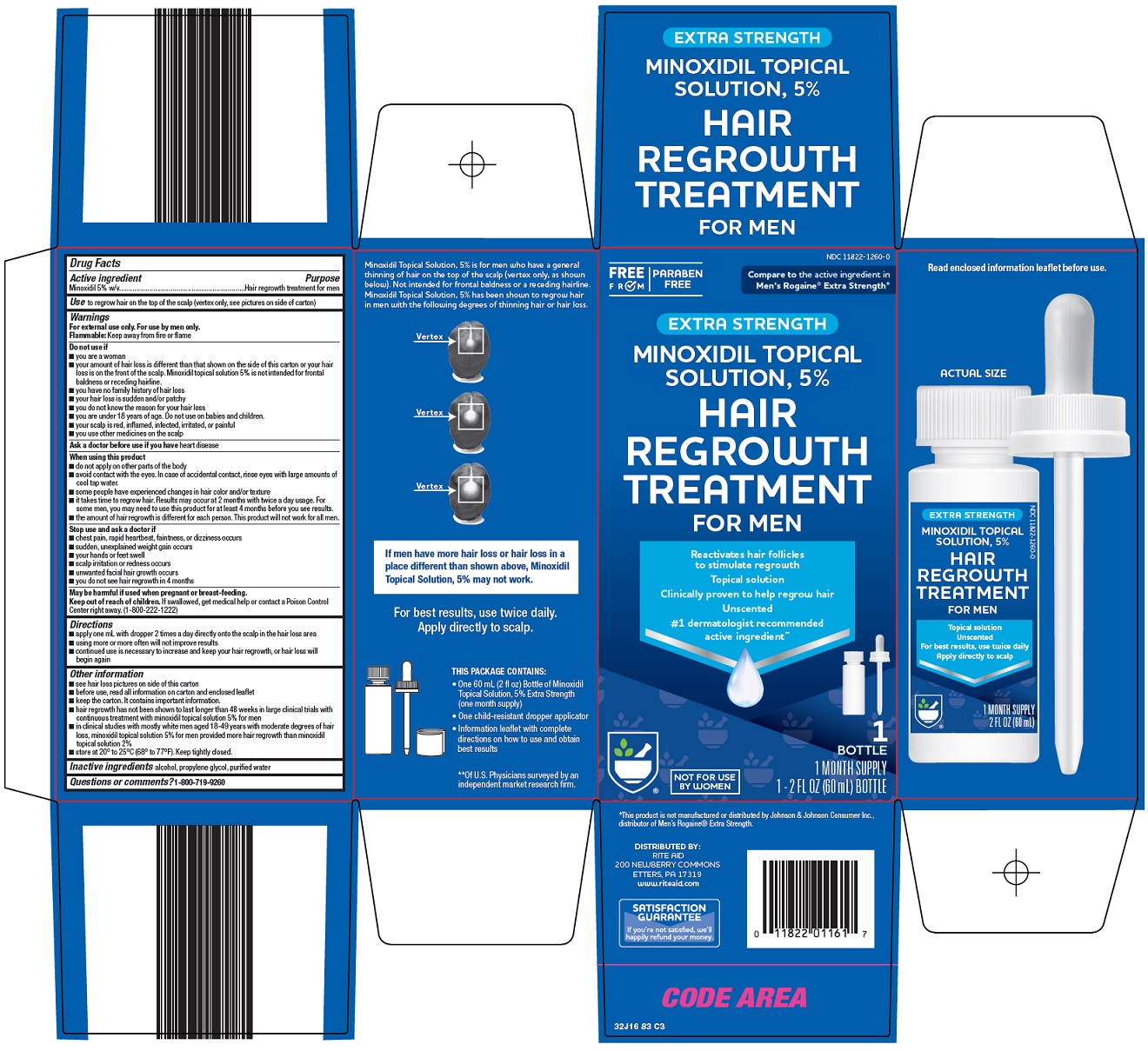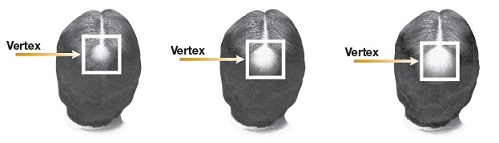 DRUG LABEL: hair regrowth treatment
NDC: 11822-1260 | Form: SOLUTION
Manufacturer: Rite Aid Corporation
Category: otc | Type: HUMAN OTC DRUG LABEL
Date: 20251008

ACTIVE INGREDIENTS: MINOXIDIL 5 g/100 mL
INACTIVE INGREDIENTS: ALCOHOL; PROPYLENE GLYCOL; WATER

Rite Aid Corporation Hair Regrowth Treatment Drug Facts

Active ingredient

Minoxidil 5% w/v

Purpose

Hair regrowth treatment for men

Use

to regrow hair on the top of the scalp (vertex only, see pictures on side of carton)

Warnings

For external use only. For use by men only.

Flammable: Keep away from fire or flame

Do not use if

- you are a woman
- your amount of hair loss is different than that shown on the side of this carton or your hair loss is on the front of the scalp. Minoxidil topical solution 5% is not intended for frontal baldness or receding hairline.
- you have no family history of hair loss
- your hair loss is sudden and/or patchy
- you do not know the reason for your hair loss
- you are under 18 years of age. Do not use on babies and children.
- your scalp is red, inflamed, infected, irritated, or painful
- you use other medicines on the scalp

Ask a doctor before use if you have

heart disease

When using this product

- do not apply on other parts of the body
- avoid contact with the eyes. In case of accidental contact, rinse eyes with large amounts of cool tap water.
- some people have experienced changes in hair color and/or texture
- it takes time to regrow hair. Results may occur at 2 months with twice a day usage. For some men, you may need to use this product for at least 4 months before you see results.
- the amount of hair regrowth is different for each person. This product will not work for all men.

Stop use and ask a doctor if

- chest pain, rapid heartbeat, faintness, or dizziness occurs
- sudden, unexplained weight gain occurs
- your hands or feet swell
- scalp irritation or redness occurs
- unwanted facial hair growth occurs
- you do not see hair regrowth in 4 months

Keep out of reach of children.

If swallowed, get medical help or contact a Poison Control Center right away. (1-800-222-1222)

Directions

- apply one mL with dropper 2 times a day directly onto the scalp in the hair loss area
- using more or more often will not improve results
- continued use is necessary to increase and keep your hair regrowth, or hair loss will begin again

Other information

- see hair loss pictures on side of this carton
- before use, read all information on carton and enclosed leaflet
- keep the carton. It contains important information.
- hair regrowth has not been shown to last longer than 48 weeks in large clinical trials with continuous treatment with minoxidil topical solution 5% for men
- in clinical studies with mostly white men aged 18-49 years with moderate degrees of hair loss, minoxidil topical solution 5% for men provided more hair regrowth than minoxidil topical solution 2%
- store at 20° to 25°C (68° to 77°F). Keep tightly closed.

Inactive ingredients

alcohol, propylene glycol, purified water

Questions or comments?

1-800-719-9260

Consumer Information

IMPORTANT INFORMATION ABOUT

Minoxidil Topical Solution USP 5%

Hair Regrowth Treatment

UNSCENTED

Extra Strength For Men

- Clinically Proven to Help Regrow Hair
- Reactivates Hair Follicles To Stimulate Regrowth
- Provides more hair regrowth than minoxidil topical solution 2%

Not For Use By Women

SAVE THIS LEAFLET FOR FUTURE REFERENCE

It takes time to regrow hair. Results may occur at 2 months with twice a day usage. For some men, you may need to use this product for at least 4 months before you see results.

Please read this leaflet carefully. It will help you understand how to use minoxidil topical solution 5% and what to expect from its use. If you have any questions after reading this leaflet, or anytime while using minoxidil topical solution 5%, you should ask your healthcare professional or call us at 1-800-719-9260.

What is minoxidil topical solution 5%?

Minoxidil topical solution 5% is a clear, light amber liquid medication containing 5% minoxidil for use only on the scalp to help regrow hair in men.

Who may use minoxidil topical solution 5%?

Minoxidil topical solution 5% is for use only by men. Minoxidil topical solution 5% may be appropriate for you if you are a male at least 18 years old and experiencing gradually thinning hair or gradual hair loss on the top of the scalp (vertex only, as shown below). It is not intended for frontal baldness or a receding hairline. The common inherited thinning or hair loss process begins slowly and may become noticeable only after years of gradual loss.

Minoxidil topical solution 5% is for men with hair loss or thinning hair that begins on the vertex of the scalp. Minoxidil topical solution 5% is more likely to regrow hair in men with hair loss in the range shown below. If men have more hair loss than shown, minoxidil topical solution 5% may not work.

Many of those experiencing hair loss have other family members with gradual thinning hair or hair loss. If you have no family history of gradual thinning hair or of gradual hair loss, or your hair loss is patchy, see your doctor.

Who should NOT use minoxidil topical solution 5%?

- Women should not use minoxidil topical solution 5% because studies have shown it works no better in women than minoxidil topical solution 2%. Some women may also grow facial hair. In addition, minoxidil topical solution 5% may be harmful if used during pregnancy or breast-feeding.
- Minoxidil topical solution 5% should not be used on babies or for children under 18 years old.
- Minoxidil topical solution 5% will not prevent or improve hair loss which may occur with the use of some prescription and non-prescription medications, certain severe nutritional problems (very low body iron; too much vitamin A intake), low thyroid states (hypothyroidism), chemotherapy, or diseases which cause scarring of the scalp.

Also, minoxidil topical solution 5% will not improve hair loss due to:

- damage from the use of hair care products which cause scarring or deep burns of the scalp.
- hair grooming methods such as cornrowing or ponytails which require pulling the hair tightly back from the scalp.

Do not use if you are not sure of the reason for your hair loss.

Will minoxidil topical solution 5% work for me?

The amount of hair regrowth is different for each person. Not everyone will respond to minoxidil topical solution 5%. The response to minoxidil topical solution 5% cannot be predicted. It is unlikely anyone will be able to grow back all their hair.

However, to see your best results with minoxidil topical solution 5%, make sure you get the medicine directly to the scalp and apply it twice a day, every day.

You may get better results if you have been losing your hair for a short period of time or have little hair loss. However, for some men minoxidil topical solution 5% may not work.

How soon can I expect results from using minoxidil topical solution 5%?

Since normal hair usually grows only 1/2 to 1 inch per month, hair regrowth with minoxidil topical solution 5% also takes time.

Results may be seen as early as 2 months with twice daily use. For some men, it may take at least 4 months for results to be seen. If you do not see any results after 4 months, stop using minoxidil topical solution 5%.

When you first begin to use minoxidil topical solution 5%, your hair loss may increase temporarily for up to 2 weeks. This is likely a sign that you are getting rid of old hairs in order to regrow more new hairs. This temporary increase in hair loss is expected and is a part of the process for how minoxidil topical solution 5% regrows hair. Remember, this increased hair loss is temporary. However, if it continues after two weeks, see your doctor.

If minoxidil topical solution 5% is working, what will the hair look like?

At first, hair growth is usually soft, downy, colorless hairs (like peach fuzz). After further use, the new hairs should be the same color and thickness as the other hairs on your scalp.

How long do I need to use minoxidil topical solution 5%?

If you experience hair regrowth, continued use of minoxidil topical solution 5% is necessary or the hair loss will begin again. In studies with minoxidil topical solution 5%, hair regrowth has not been shown to last longer than 48 weeks of continuous treatment in large clinical trials.

What happens if I completely stop using minoxidil topical solution 5%?

Will I keep the new hair?

Continuous use of minoxidil topical solution 5% is needed to maintain hair regrowth.

If you stop using minoxidil topical solution 5%, you will lose your newly regrown hair in 3 to 4 months.

How do I use minoxidil topical solution 5%?

For best results, apply 1 mL with applicator 2 times a day directly onto the scalp in the hair loss area. Using more or using more often will not improve results. Each bottle should last one month, if used as directed.

Allow time for minoxidil topical solution 5% to dry completely before wearing a hat, or lying on a pillow, etc. Minoxidil topical solution 5% may cause staining of clothing or linens if damp on the scalp. When applying minoxidil topical solution 5% at night, be sure to allow 2 to 4 hours to dry completely. Never take this product by mouth or apply to other parts of the body.

When do I use minoxidil topical solution 5%?

Apply minoxidil topical solution 5% once in the morning and once at night. The nighttime application should occur 2 to 4 hours before going to bed to allow for drying. Each bottle should last one month, if used as directed.

What if I miss a dose or forget to use minoxidil topical solution 5%?

If you miss one or two daily doses of minoxidil topical solution 5%, just continue with your next dose. You should not make up for missed doses.

Can I use minoxidil topical solution 5% more than twice a day? Will it work faster, better?

No. Minoxidil topical solution 5% will not work faster or better if used more than two times a day. Studies have been carefully conducted to determine the correct amount of minoxidil topical solution 5% needed to get the best results. More frequent use or larger doses have not been shown to speed up hair growth and may increase your chance of side effects.

What kind of shampoo should I use with minoxidil topical solution 5%?

If you wash your scalp before applying minoxidil topical solution 5%, use a mild shampoo.

Can I use hair sprays, mousses, conditioners, gels, etc.?

Yes. Hair sprays, spritz, or styling aids may be used on your hair while using minoxidil topical solution 5%. For best results, minoxidil topical solution 5% should be allowed to soak into the scalp before using any styling products. Try to develop a good routine of applying minoxidil topical solution 5% first, and then applying styling products and style as usual. Keep in mind that your best results will be seen with proper application.

Can I have my hair colored or permed or use hair relaxers while using minoxidil topical solution 5%?

Yes. We have no evidence that coloring or perming your hair or that the use of relaxers change the effect of minoxidil topical solution 5%. However, because the use of a permanent wave and hair color can cause scalp irritation on certain people, we recommend the following precautions:

1) To avoid possible scalp irritation, you should make sure all of the minoxidil topical solution 5% has been washed off the hair and scalp before using color or perm chemicals.
2) For best results, do not apply minoxidil topical solution 5% on the same day that you use a chemical treatment on your hair.
3) Do not use minoxidil topical solution 5% for 24 hours after using any chemicals to make sure your scalp has not been irritated by the perm or color treatment. If no irritation occurs, continue use of minoxidil topical solution 5% as usual.
4) Simply restart your normal minoxidil topical solution 5% routine. There is no need to use more minoxidil topical solution 5% to make up for missed applications. Missing one day of minoxidil topical solution 5% will not affect your hair regrowth results.

Can I apply minoxidil topical solution 5% and wash my hair an hour later?

No. For minoxidil topical solution 5% to work best, you should allow it to stay on the scalp for about 4 hours before washing.

Directions for Use

1) Remove the cap. To remove, push down and turn in direction of the arrows on the cap.
2) Part your hair in the area of hair thinning/loss. Follow the instructions below for using the dropper applicator and apply one mL 2 times a day directly onto the scalp in the hair loss area. Do not use more. Spread the liquid evenly over the hair loss area. If you use your fingers, wash hands with soap and water immediately. Each bottle should last about one month, if used as directed. Use a mild shampoo if you wash your scalp before applying minoxidil topical solution 5%.

Using the Dropper Applicator

1) Squeeze the rubber bulb and insert the dropper into the bottle. Release the bulb, allowing the dropper to fill to the 1 mL line. If the level of the solution is above the 1 mL line, squeeze the extra amount back into the bottle.
2) Next, place the tip of the dropper near the part of the scalp you want to treat and gently squeeze the bulb to gradually release the solution. To prevent the solution from running off the scalp, apply a small amount at a time.
3) After each use attach the dropper to the bottle to make it child-resistant by turning it clockwise until tightly closed.

Warnings

For external use only

For use by men only

Flammable: Keep away from fire or flame

Do not use if

- you are a woman
- your amount of hair loss is different than that shown on the other side of this leaflet or your hair loss is on the front of the scalp. Minoxidil topical solution 5% is not intended for frontal baldness or receding hairline.
- you have no family history of hair loss
- your hair loss is sudden and/or patchy
- you do not know the reason for your hair loss
- you are under 18 years of age. Do not use on babies and children.
- scalp is red, inflamed, infected, irritated, or painful
- you use other medicines on the scalp

Ask a doctor before use if you have heart disease.

When using this product

- do not apply on other parts of the body
- avoid contact with the eyes. In case of accidental contact, rinse eyes with large amounts of cool tap water.
- some people have experienced changes in hair color and/or texture
- it takes time to regrow hair. Results may occur at 2 months with twice a day usage. For some men, you may need to use this product for at least 4 months before you see results.
- the amount of hair regrowth is different for each person. This product will not work for all men.

Stop use and ask a doctor if

- chest pain, rapid heartbeat, faintness, or dizziness occurs
- sudden, unexplained weight gain occurs
- your hands or feet swell
- scalp irritation or redness occurs
- unwanted facial hair growth occurs
- you do not see hair regrowth in 4 months

May be harmful if used when pregnant or breast-feeding.

Keep out of reach of children. If swallowed, get medical help or contact a Poison Control Center right away. (1-800-222-1222)

What are the most common side effects with minoxidil topical solution 5%?

The most common side effects are itching and skin irritation of the treated area of the scalp. If scalp irritation continues, stop use and see a doctor. Minoxidil topical solution 5% contains alcohol, which will cause burning or irritation of the eyes. If minoxidil topical solution 5% accidentally gets into eyes, rinse with large amounts of cool tap water.

Can minoxidil topical solution 5% produce unwanted hair growth?

Unwanted hair growth on the face and other parts of the body has been reported in women. But it is rare and reversible. If you develop unwanted hair, stop using minoxidil topical solution 5%. Over time, the unwanted hair, if caused by minoxidil topical solution 5%, will go away. You can take the following steps to decrease the chances of unwanted hair growth:

1) limit the application of minoxidil topical solution 5% only to the scalp;
2) if you use your hands to apply minoxidil topical solution 5%, wash your hands well immediately afterwards; and
3) after your nighttime application of minoxidil topical solution 5%, allow enough drying time before going to bed (usually 2 to 4 hours).

Can I use minoxidil topical solution 5% for baldness or hair loss in babies or children?

No. Minoxidil topical solution 5% must not be used to treat baldness or hair loss in babies and children.

If you have any other questions, ask your healthcare professional or call us at 1-800-719-9260.

Store at 20º to 25ºC (68º to 77ºF). Keep tightly closed.

Packaged By

Perrigo®

Allegan, MI 49010

Rev 10-19

32J0000J1

Package/Label Principal Display Panel

FREE FROM | PARABEN FREE

Compare to the active ingredient in Men’s Rogaine® Extra Strength

EXTRA STRENGTH

MINOXIDIL TOPICAL SOLUTION, 5%

HAIR REGROWTH TREATMENT

FOR MEN

Reactivates hair follicles to stimulate regrowth

Topical solution

Clinically proven to help regrow hair

Unscented

#1 dermatologist recommended active ingredient

NOT FOR USE BY WOMEN

1 BOTTLE

1 MONTH SUPPLY

1 – 2 FL OZ (60 mL) BOTTLE